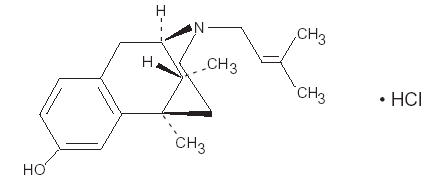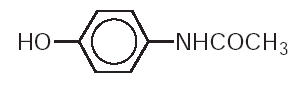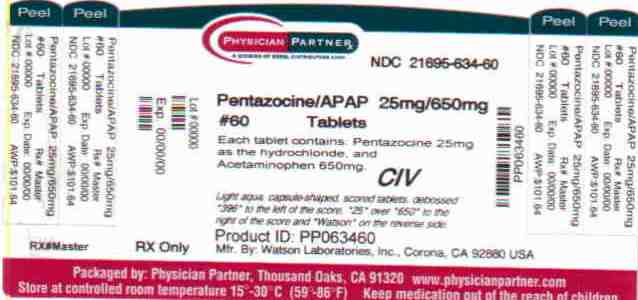 DRUG LABEL: Pentazocine HCl and Acetaminophen
NDC: 21695-634 | Form: TABLET
Manufacturer: Rebel Distributors Corp
Category: prescription | Type: HUMAN PRESCRIPTION DRUG LABEL
Date: 20101110
DEA Schedule: CIV

ACTIVE INGREDIENTS: Pentazocine hydrochloride 25 mg/1 1; Acetaminophen 650 mg/1 1
INACTIVE INGREDIENTS: SILICON DIOXIDE; CROSPOVIDONE; D&C YELLOW NO. 10; FD&C BLUE NO. 1; CELLULOSE, MICROCRYSTALLINE; POVIDONE; STARCH, CORN; SODIUM STARCH GLYCOLATE TYPE A POTATO; stearic acid

Pentazocine HCl
and
Acetaminophen
Tablets C-IV
Rx only
30276-4

DESCRIPTION

Pentazocine hydrochloride and acetaminophen tablets are a combination of pentazocine hydrochloride USP, equivalent to 25 mg base and acetaminophen USP, 650 mg.

Pentazocine is a member of the benzazocine series (also known as the benzomorphan series). Chemically, pentazocine hydrochloride is (2R*,6R*,11R*)-1,2,3,4,5,6-hexahydro-6,11-dimethyl-3-(3-methyl-2-butenyl)-2,6-methano-3-benzazocin-8-ol hydrochloride, a white, crystalline substance soluble in acidic aqueous solutions. It has the following structural formula:

C19H27NO•HCl Molecular Weight: 321.88

Chemically, acetaminophen is 4’-hydroxyacetanilide-. It has the following structural formula:

C8H9NO2 Molecular Weight: 151.16

Pentazocine is an analgesic and acetaminophen is an analgesic and antipyretic.

Each tablet for oral administration contains 25 mg of pentazocine as the hydrochloride and 650 mg of acetaminophen. In addition, each tablet contains the following inactive ingredients: colloidal silicon dioxide, crospovidone, D&C Yellow No. 10 Aluminum Lake, FD&C Blue No. 1 Aluminum Lake, microcrystalline cellulose, povidone, pregelatinized starch, sodium starch glycolate, and stearic acid.

CLINICAL PHARMACOLOGY

Pentazocine hydrochloride and acetaminophen tablets are an analgesic possessing antipyretic actions.

Pentazocine is an analgesic with agonist/antagonist action which when administered orally is approximately equivalent on a mg for mg basis in analgesic effect to codeine.

Acetaminophen is an analgesic and antipyretic.

Onset of significant analgesia with pentazocine usually occurs between 15 and 30 minutes after oral administration, and duration of action is usually three hours or longer. Onset and duration of action and the degree of pain relief are related both to dose and the severity of pretreatment pain. Pentazocine weakly antagonizes the analgesic effects of morphine, meperidine, and phenazocine; in addition, it produces incomplete reversal of cardiovascular, respiratory, and behavioral depression induced by morphine and meperidine. Pentazocine has about 1/50 the antagonistic activity of nalorphine. It also has a sedative activity.

Pentazocine is well absorbed from the gastrointestinal tract. Plasma levels closely correspond to the onset, duration, and intensity of analgesia. The time to mean peak concentration in 24 normal volunteers was 1.7 hours (range 0.5 to 4 hours) after oral administration and the mean plasma elimination half-life was 3.6 hours (range 1.5 to 10 hours).

The action of pentazocine is terminated for the most part by biotransformation in the liver with some free pentazocine excreted in the urine. The products of the oxidation of the terminal methyl groups and glucuronide conjugates are excreted by the kidney. Elimination of approximately 60% of the total dose occurs within 24 hours. Pentazocine passes the placental barrier.

Onset of significant analgesic and antipyretic activity of acetaminophen when administered orally occurs within 30 minutes and is maximal at approximately 2^1/2 hours. The pharmacological mode of action of acetaminophen is unknown at this time.

Acetaminophen is rapidly and almost completely absorbed from the gastrointestinal tract. In 24 normal volunteers the mean time to peak plasma concentration was 1 hour (range 0.25 to 3 hours) after oral administration and the mean plasma elimination half-life was 2.8 hours (range 2 to 4 hours).

The effect of pentazocine on acetaminophen plasma protein binding or vice versa has not been established. For acetaminophen there is little or no plasma protein binding at normal therapeutic doses. When toxic doses of acetaminophen are ingested and drug plasma levels exceed 90 mcg/mL, plasma binding may vary from 8% to 43%.

Acetaminophen is conjugated in the liver with glucuronic acid and to a lesser extent with sulfuric acid. Approximately 80% of acetaminophen is excreted in the urine after conjugation and about 3% is excreted unchanged. The drug is also conjugated to a lesser extent with cysteine and additionally metabolized by hydroxylation.

If pentazocine hydrochloride and acetaminophen tablets are taken every 4 hours over an extended period of time, accumulation of pentazocine and to a lesser extent, acetaminophen, may occur.

INDICATIONS AND USAGE

Pentazocine hydrochloride and acetaminophen tablets are indicated for the relief of mild to moderate pain.

CONTRAINDICATIONS

Pentazocine hydrochloride and acetaminophen tablets should not be administered to patients who are hypersensitive to either pentazocine or acetaminophen.

WARNINGS

Head Injury and Increased Intracranial Pressure. As in the case of other potent analgesics, the potential of pentazocine for elevating cerebrospinal fluid pressure may be attributed to CO2 retention due to the respiratory depressant effects of the drug. These effects may be markedly exaggerated in the presence of head injury, other intracranial lesions, or a pre-existing increase in intracranial pressure. Furthermore, pentazocine can produce effects which may obscure the clinical course of patients with head injuries. In such patients, pentazocine hydrochloride and acetaminophen tablets must be used with extreme caution and only if its use is deemed essential.

Acute CNS Manifestations. Patients receiving therapeutic doses of pentazocine have experienced hallucinations (usually visual), disorientation, and confusion which have cleared spontaneously within a period of hours. The mechanism of this reaction is not known. Such patients should be closely observed and vital signs checked. If the drug is reinstituted, it should be done with caution since these acute CNS manifestations may recur.

There have been instances of psychological and physical dependence on parenteral pentazocine in patients with a history of drug abuse, and rarely, in patients without such a history. (SeeDRUG ABUSE AND DEPENDENCE.)

Due to the potential for increased CNS depressant effects, alcohol should be used with caution in patients who are currently receiving pentazocine.

Pentazocine may precipitate opioid abstinence symptoms in patients receiving courses of opiates for pain relief.

PRECAUTIONS

In prescribing pentazocine hydrochloride and acetaminophen tablets for chronic use, the physician should take precautions to avoid increases in dose by the patient.

Myocardial Infarction

As with all drugs, pentazocine hydrochloride and acetaminophen tablets should be used with caution in patients with myocardial infarction who have nausea or vomiting.

Certain Respiratory Conditions

Although respiratory depression has rarely been reported after oral administration of pentazocine, the drug should be administered with caution to patients with respiratory depression from any cause, severely limited respiratory reserve, severe bronchial asthma and other obstructive respiratory conditions, or cyanosis.

Impaired Renal or Hepatic Function

Decreased metabolism of the drug by the liver in extensive liver disease may predispose to accentuation of side effects. Although laboratory tests have not indicated that pentazocine causes or increases renal or hepatic impairment, the drug should be administered with caution to patients with such impairment.

Since acetaminophen is metabolized by the liver, the question of the safety of its use in the presence of liver disease should be considered.

Biliary Surgery

Narcotic drug products are generally considered to elevate biliary tract pressure for varying periods following their administration. Some evidence suggests that pentazocine may differ from other marketed narcotics in this respect (i.e., it causes little or no elevation in biliary tract pressures). The clinical significance of these findings, however, is not yet known.

CNS Effect

Caution should be used when pentazocine hydrochloride and acetaminophen tablets are administered to patients prone to seizures; seizures have occurred in a few such patients in association with the use of pentazocine although no cause and effect relationship has been established.

Information for Patients

Since sedation, dizziness, and occasional euphoria have been noted, ambulatory patients should be warned not to operate machinery, drive cars, or unnecessarily expose themselves to hazards. Pentazocine may cause physical and psychological dependence when taken alone and may have additive CNS depressant properties when taken in combination with alcohol or other CNS depressants.

Drug Interactions

Pentazocine is a mild narcotic antagonist. Some patients previously given narcotics, including methadone for the daily treatment of narcotic dependence, have experienced withdrawal symptoms after receiving pentazocine.

Carcinogenesis, Mutagenesis, Impairment of Fertility

Carcinogenesis, mutagenesis, and impairment of fertility studies have not been done with this combination product.

Pentazocine, when administered orally or parenterally, had no adverse effect on either the reproductive capabilities or the course of pregnancy in rabbits and rats. Embryotoxic effects on the fetuses were not shown.

The daily administration of 4 mg/kg to 20 mg/kg pentazocine subcutaneously to female rats during a 14 day pre-mating period and until the 13th day of pregnancy did not have any adverse effects on the fertility rate.

There is no evidence in long-term animal studies to demonstrate that pentazocine is carcinogenic.

Pregnancy Category C

Animal reproduction studies have not been conducted with pentazocine hydrochloride and acetaminophen tablets. It is also not known whether pentazocine hydrochloride and acetaminophen tablets can cause fetal harm when administered to pregnant women or can affect reproduction capacity. Pentazocine hydrochloride and acetaminophen tablets should be given to pregnant women only if clearly needed. However, animal reproduction studies with pentazocine have not demonstrated teratogenic or embryotoxic effects.

Nonteratogenic Effects

There has been no experience in this regard with the combination pentazocine and acetaminophen. However, there have been rare reports of possible abstinence syndromes in newborns after prolonged use of pentazocine during pregnancy.

Labor and Delivery

Patients receiving pentazocine during labor have experienced no adverse effects other than those that occur with commonly used analgesics. Pentazocine hydrochloride and acetaminophen tablets should be used with caution in women delivering premature infants. The effect of pentazocine hydrochloride and acetaminophen tablets on the mother and fetus, the duration of labor or delivery, the possibility that forceps delivery or other intervention or resuscitation of the newborn may be necessary, or the effect of pentazocine hydrochloride and acetaminophen tablets on the later growth, development, and functional maturation of the child are unknown at the present time.

Nursing Mothers

It is not known whether this drug is excreted in human milk. Because many drugs are excreted in human milk, caution should be exercised when pentazocine hydrochloride and acetaminophen tablets are administered to a nursing woman.

Pediatric Use

Safety and effectiveness in pediatric patients below the age of 12 have not been established.

Geriatric Use

Clinical studies of pentazocine hydrochloride and acetaminophen tablets did not include sufficient numbers of subjects aged 65 and over to determine whether they respond differently from younger subjects. Other reported clinical experience has not identified differences in responses between the elderly and younger patients. In general, dose selection for an elderly patient should be cautious, usually starting at the low end of the dosing range, reflecting the greater frequency of decreased hepatic, renal, or cardiac function, and of concomitant disease or other drug therapy.

ADVERSE REACTIONS

Clinical experience with pentazocine hydrochloride and acetaminophen tablets has been insufficient to define all possible adverse reactions with this combination. However, reactions reported after oral administration of pentazocine hydrochloride in 50 mg dosage include gastrointestinal: nausea, vomiting, infrequently constipation; and rarely abdominal distress, anorexia, diarrhea. CNS effects: dizziness, lightheadedness, hallucinations, sedation, euphoria, headache, confusion, disorientation; infrequently weakness, disturbed dreams, insomnia, syncope, visual blurring and focusing difficulty, depression; and rarely tremor, irritability, excitement, tinnitus. Autonomic: sweating; infrequently flushing; and rarely chills. Allergic: infrequently rash; and rarely urticaria, edema of the face. Cardiovascular: infrequently decrease in blood pressure, tachycardia. Hematologic: rarely depression of white blood cells (especially granulocytes), which is usually reversible, moderate transient eosinophilia. Other: rarely respiratory depression, urinary retention, paresthesia, serious skin reactions, including erythema multiforme, Stevens-Johnson Syndrome, toxic epidermal necrolysis, and in one instance, an apparent anaphylactic reaction has been reported.

Numerous clinical studies have shown that acetaminophen, when taken in recommended doses, is relatively free of adverse effects in most age groups, even in the presence of a variety of disease states.

A few cases of hypersensitivity to acetaminophen have been reported, as manifested by skin rashes, thrombocytopenic purpura, rarely hemolytic anemia and agranulocytosis. Occasional individuals respond to ordinary doses with nausea and vomiting and diarrhea.

DRUG ABUSE AND DEPENDENCE

Controlled Substance. The combination of pentazocine hydrochloride and acetaminophen tablets is a Schedule IV controlled substance.

Abuse and Dependence. There have been some reports of dependence and of withdrawal symptoms with orally administered pentazocine. There have been recorded instances of psychological and physical dependence in patients using parenteral pentazocine. Abrupt discontinuance following the extended use of parenteral pentazocine has resulted in withdrawal symptoms. Patients with a history of drug dependence should be under close supervision while receiving pentazocine hydrochloride and acetaminophen tablets. There have been rare reports of possible abstinence syndromes in newborns after prolonged use of pentazocine during pregnancy.

Some tolerance to the analgesic and subjective effects of pentazocine develops with frequent and repeated use.

Drug addicts who are given closely spaced doses of pentazocine (e.g., 60 mg to 90 mg every 4 hours) develop physical dependence which is demonstrated by abrupt withdrawal or by administration of naloxone. The withdrawal symptoms exhibited after chronic doses of more than 500 mg of pentazocine per day have similar characteristics, but to a lesser degree, of opioid withdrawal and may be associated with drug seeking behavior.

OVERDOSAGE

Manifestations

Clinical experience with pentazocine hydrochloride and acetaminophen tablets has been insufficient to define the signs of overdosage with this product. It may be assumed that signs and symptoms of pentazocine hydrochloride and acetaminophen tablets overdose would be a combination of those observed with pentazocine overdose and acetaminophen overdose.

For pentazocine alone in single doses above 60 mg there have been reports of the occurrence of nalorphine-like psychotomimetic effects such as anxiety, nightmares, strange thoughts, and hallucinations. Marked respiratory depression associated with increased blood pressure and tachycardia have also resulted from excessive doses as have dizziness, nausea, vomiting, lethargy, and paresthesias. The respiratory depression is antagonized by naloxone (see Treatment).

In acute acetaminophen overdosage, dose-dependent, potentially fatal hepatic necrosis is the most serious adverse effect. Renal tubular necrosis, hypoglycemic coma, and thrombocytopenia may also occur.

In adults, a single dose of 10 g to 15 g (200 mg/kg to 250 mg/kg) of acetaminophen may cause hepatotoxicity. A dose of 25 g or more is potentially fatal. The potential seriousness of the intoxication may not be evident during the first two days of acute acetaminophen poisoning. During the first 24 hours, nausea, vomiting, anorexia, and abdominal pain occur. These may persist for a week or more. Liver injury may become evident the second day, initial signs being elevation of the serum transaminase and lactic dehydrogenase activity, increased serum bilirubin concentration, and prolongation of prothrombin time. Serum albumin concentration and alkaline phosphatase activity may remain normal. The hepatotoxicity may lead to encephalopathy, coma, and death. Transient azotemia is evident in a majority of patients and acute renal failure occurs in some.

There have been reports of glycosuria and impaired glucose tolerance, but hypoglycemia may also occur. Metabolic acidosis and metabolic alkalosis have been reported. Cerebral edema and nonspecific myocardial depression have also been noted. Biopsy reveals centrolobular necrosis with sparing of the periportal area. The hepatic lesions are reversible over a period of weeks or months in nonfatal cases.

The severity of the liver injury can be determined by measurement of the plasma halftime of acetaminophen during the first day of acute poisoning. If the halftime exceeds 4 hours, hepatic necrosis is likely and if the halftime is greater than 12 hours, hepatic coma will probably occur. Only minimal liver damage has developed when the serum concentration was below 120 mcg/mL at 12 hours after ingestion of the drug. If serum bilirubin concentration is greater than 4 mg/100 mL during the first 5 days, encephalopathy may occur.

The seven day oral LD50 value for pentazocine hydrochloride and acetaminophen tablets in mice is 3,570 mg/kg.

Treatment

Oxygen, intravenous fluids, vasopressors, and other supportive measures should be employed as indicated. Assisted or controlled ventilation should also be considered. For respiratory depression due to overdosage or unusual sensitivity to pentazocine hydrochloride and acetaminophen tablets, parenteral naloxone is a specific and effective antagonist.

The toxic effects of acetaminophen may be prevented or minimized by antidotal therapy with N-acetylcysteine. In order to obtain the best possible results, N-acetylcysteine should be administered within approximately 16 hours of ingestion of the overdose.

For complete prescribing information for the approved use of acetylcysteine in the treatment of acetaminophen overdose, see the package insert for acetylcysteine.

Vigorous supportive therapy is required in severe intoxication. Procedures to limit the continuing absorption of the drug must be readily performed since the hepatic injury is dose dependent and occurs early in the course of intoxication. Induction of vomiting or gastric lavage, followed by oral administration of activated charcoal should be done in all cases.

If hemodialysis can be initiated within the first 12 hours, it is advocated for patients with a plasma acetaminophen concentration exceeding 120 mcg/mL at 4 hours after ingestion of the drug.

DOSAGE AND ADMINISTRATION

Adult. The usual adult dose is 1 tablet every 4 hours as needed for pain relief, up to maximum of 6 tablets per day.

The usual duration of therapy is dependent upon the condition being treated but in any case should be reviewed regularly by the physician. The effect of meals on the rate and extent of bioavailability of both pentazocine and acetaminophen has not been documented.

HOW SUPPLIED

Pentazocine Hydrochloride and Acetaminophen Tablets, 25 mg base/650 mg are light aqua, capsule-shaped, scored tablets, debossed 396 to the left of the score, 25 over 650 to the right of the score and WATSON on the reverse side supplied in bottles of 100.

Store at controlled room temperature 15°-30°C (59°-86°F). [See USP.]

Dispense in a tight, light-resistant container as defined in the USP.

Watson Laboratories, Inc.
Corona, CA 92880 USA

30276-4
Revised: February 2004

Repackaged by:

Rebel Distributors Corp

Thousand Oaks, CA 91320